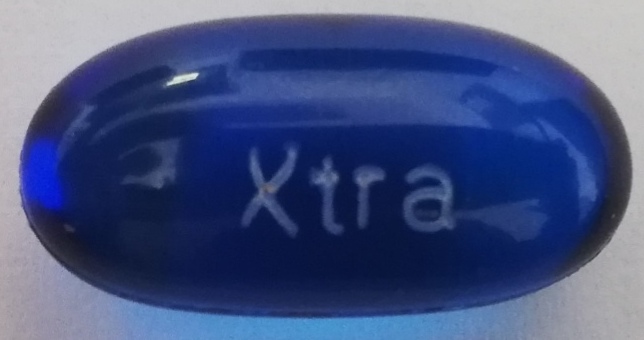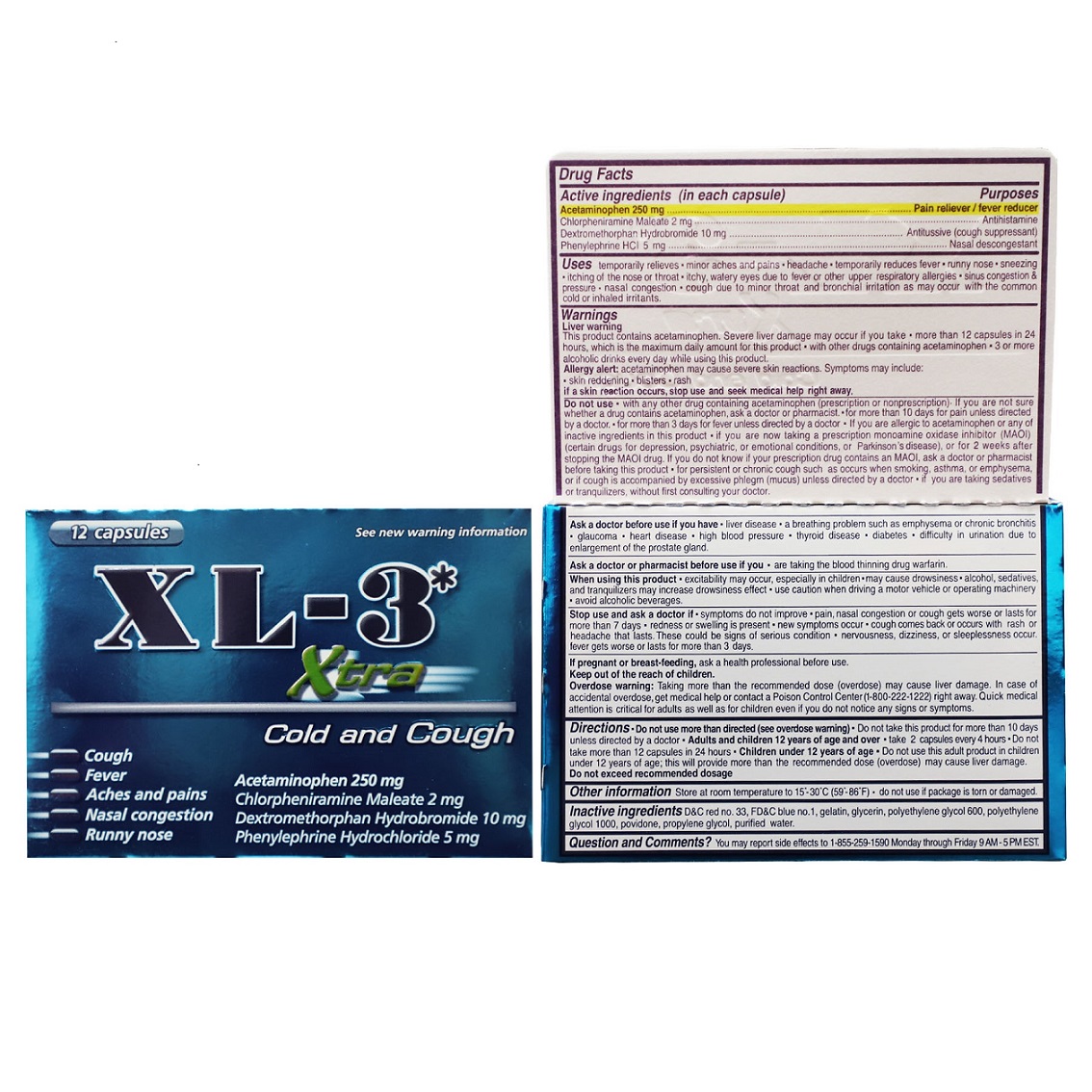 DRUG LABEL: Cough and Cold
NDC: 63654-800 | Form: CAPSULE, LIQUID FILLED
Manufacturer: Selder, S.A. de C.V.
Category: otc | Type: HUMAN OTC DRUG LABEL
Date: 20241017

ACTIVE INGREDIENTS: ACETAMINOPHEN 250 mg/1 1; PHENYLEPHRINE HYDROCHLORIDE 5 mg/1 1; CHLORPHENIRAMINE MALEATE 2 mg/1 1; DEXTROMETHORPHAN HYDROBROMIDE 10 mg/1 1
INACTIVE INGREDIENTS: D&C RED NO. 33; FD&C BLUE NO. 1; GELATIN; GLYCERIN; POLYETHYLENE GLYCOL 600; POLYETHYLENE GLYCOL 1000; POVIDONE; PROPYLENE GLYCOL; WATER

XL3LqijelActmnphnChlrphnrminDxtrmthrphnPhnylphrn

Active ingredients (in each capsule)

Acetaminophen 250 mg

Chlorpheniramine Maleate 2 mg

Dextromethorphan Hydrobromide 10 mg

Phenylephrine HCl 5 mg

Purpose

Pain reliever/fever reducer

Antihistamine

Antitussive

Nasal decongestant

Uses

temporarily relieves: • muscular aches and pains • headache • temporarily reduces fever • runny nose • sneezing • itching of the nose or throat • itchy, watery eyes due to hay fever or other upper respiratory allergies • pressure • nasal congestion • cough due to minor throat and bronchial irritation as may occur with the common cold or inhaled irritants

Warnings

Liver warning This product contains acetaminophen. Severe liver damage may occur if you take • more than 12 tablets in 24 hours, which is the maximum daily amount • with other drugs containing acetaminophen • 3 or more alcoholic drinks every day while using this product.

Allergy alert: acetaminophen may cause severe skin reactions. Symptoms may include:

• skin reddening • blisters • rash

if a skin reaction occurs, stop use and seek medical help right away.

Do not use

• with any other drug containing acetaminophen (prescription or nonprescription). If you are not sure whether a drug contains acetaminophen, ask a doctor or pharmacist. • for more than 10 days for pain unless directed by a doctor • for more than 3 days for fever unless directed by a doctor •if you are allergic to acetaminophen or any of the inactive ingredients in this product

• if you are now taking a prescription monoamine oxidase inhibitor (MAOI) (certain drugs for depression, psychiatric, or emotional conditions, or Parkinson's disease), or for 2 weeks after stopping the MAOI drug. If you do not know if your prescription drug contains an MAOI, ask a doctor or pharmacist before taking this product • for persistent or chronic cough such as occurs when smoking, asthma, or emphysema, or if cough is accompanied by excessive phlegm (mucus) unless directed by a doctor • if you are taking sedatives or tranquilizers, without first consulting your doctor.

Ask a doctor before use if you have

• liver disease • a breathing problem such as emphysema • glaucoma • heart disease • high blood pressure • thyroid disease • diabetes • difficulty in urination due to enlargement of the prostate gland

Ask a doctor or pharmacist before use if you

• are taking the blood thinning drug warfarin

When using this product

• excitability may occur, especially in children • may cause drowsiness •alcohol, sedatives and tranquilizers may increase drowsiness effect • use caution when driving a motor vehicle or operating machinery • avoid alcohlic beverages

Stop use and aska doctor

• symptoms do not improve • pain, nasal congestion or cough gets worse or lasts more than 7 days • redness or swelling is present • new symptoms occur •cough comes back or occurs with a rash or a headache tha lasts. These could be the signs of a serious condition • nervousness, dizziness, or sleeplessness occur • fever gets worse or lasts for more than 3 days.

Keep out of reach of children

If pregnant or breast-feeding, ask a health professional before use.

Keep out of the reach of children.

Overdose warning: Taking more than the recommended dose (overdose) may cause liver damage. In case of overdose, get medical help or contact a Poison Control Center (1-800-222-1222) right away. Quick medical attention is critical for adults as well as for children even if you do not notice any signs or symptoms

Directions

• Do not use more than directed (see overdose warning) •do not take this product form more than 10 days unless directed by a doctor • Adults and children 12 years of age and over • take 2 capsule every 4 hours. • Do not take more than 12 capsules in 24 hours Children under 12 years of age • Do not use this adult product in children under 12 years of age; this will provide more than the recommended dose (overdoes) may cause liver damage. Do not exceed recommended dosage

Other information

Store at room temperature to 15º-30ºC (59º-86ºF) • do not use if package is torn or damaged

Inactive ingredients

D&C red no. 33, FD&C blue no. 1, gelatin, glycerin, polyethylene glycol 600, polyethylene glycol 1000, povidone, propylene glycol, purified water

Questions and Comments?

You may report any side effects to 1-855-259-1590 Monday through Friday 9AM-5PM EST